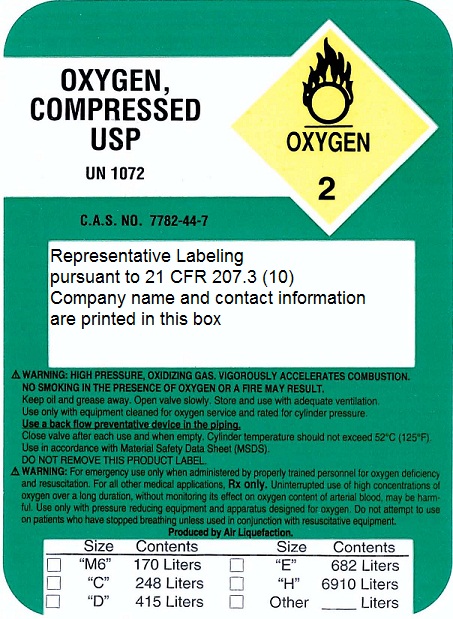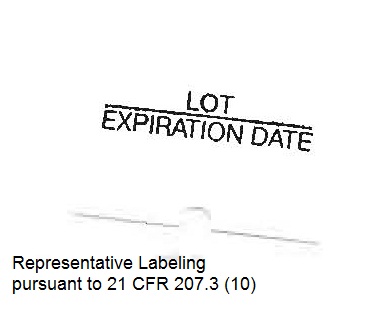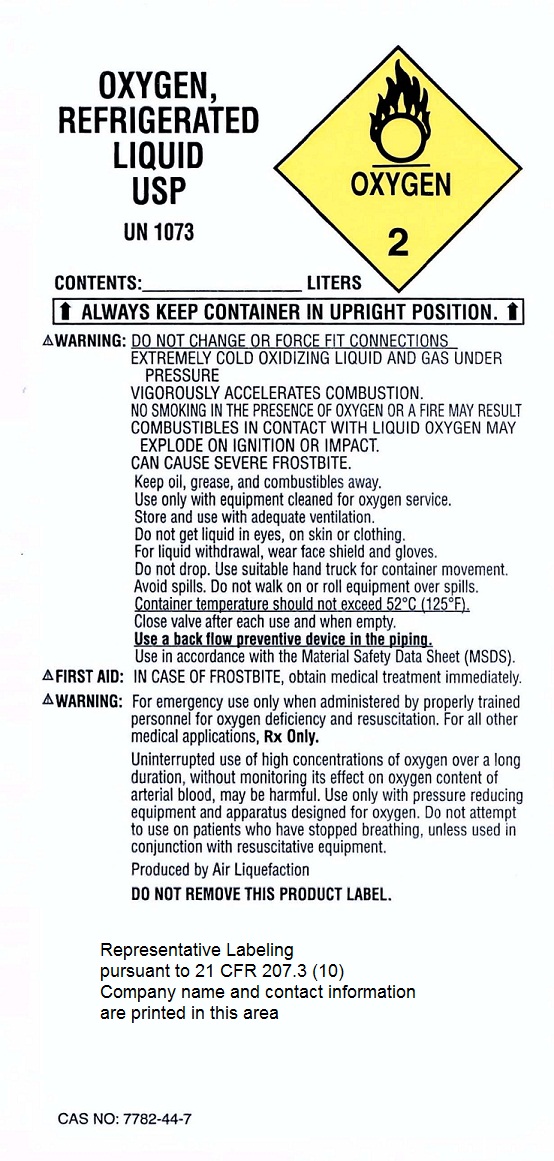 DRUG LABEL: Oxygen
NDC: 64656-0250 | Form: GAS
Manufacturer: Mercy Home Care-HME
Category: prescription | Type: HUMAN PRESCRIPTION DRUG LABEL
Date: 20101005

ACTIVE INGREDIENTS: Oxygen 99 L/100 L

Oxygen

Principal for Oxygen Product

Representative labeling